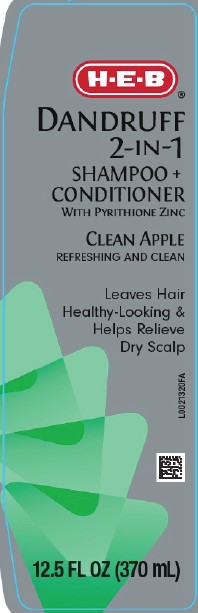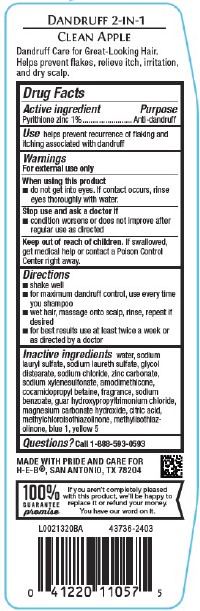 DRUG LABEL: 2 in 1 Dandruff
NDC: 37808-612 | Form: SHAMPOO
Manufacturer: H E B
Category: otc | Type: HUMAN OTC DRUG LABEL
Date: 20260224

ACTIVE INGREDIENTS: PYRITHIONE ZINC 10 mg/1 mL
INACTIVE INGREDIENTS: WATER; SODIUM LAURYL SULFATE; SODIUM LAURETH SULFATE; GLYCOL DISTEARATE; SODIUM CHLORIDE; ZINC CARBONATE; SODIUM XYLENESULFONATE; AMODIMETHICONE (800 CST); COCAMIDOPROPYL BETAINE; SODIUM BENZOATE; GUAR HYDROXYPROPYLTRIMONIUM CHLORIDE (1.7 SUBSTITUENTS PER SACCHARIDE); MAGNESIUM CARBONATE HYDROXIDE; CITRIC ACID MONOHYDRATE; METHYLCHLOROISOTHIAZOLINONE; METHYLISOTHIAZOLINONE; FD&C BLUE NO. 1; FD&C YELLOW NO. 5

HEB 612.001/612AC-AF
Clean Apple Dandruff Shampoo and Conditioner

Claims

DANDRUFF 2-IN-1

CLEAN APPLE

Dandruff Care for Great-Looking Hair.

Helps prevent flakes, relieve itch, irritation, and dry scalp.

Active ingredient

Pyrithione zinc 1%

Purpose

Anti-dandruff

Use

helps prevent recurrence of flaking and itching associated with dandruff

Warnings

For external use only

When using this product

- do not get into eyes. If contact occurs, rinse eyes thoroughly with water.

Stop use and ask a doctor if

- condition worsens or does not improve after regular use as directed

Keep out of reach of children.

If swallowed, get medical help or contact a Poison Control Center right away.

Directions

- shake well
- for maximum dandruff control, use every time you shampoo
- wet hair, massage onto scalp, rinse, repeat if desired
- for best results use at least twice a week or as directed by a doctor

Inactive ingredients

water, sodium lauryl sulfate, sodium laureth sulfate, glycol distearate, sodium chloride, zinc carbonate, sodium xylenesulfonate, amodimethicone, cocamidopropyl betaine, fragrance, sodium benzoate, guar hydroxypropyltrimonium chloride, magnesium carbonate hydroxide, citric acid, methylchloroisothiazolinone, methylisothiazolinone, blue 1, yellow 5

Questions?

Call 1-888-593-0593

ADVERSE REACTION

MADE WITH PRIDE AND CARE FOR H-E-B®, SAN ANTONIO, TX 78204

100% GUARANTEE

If you aren't completely pleased with this product, we'll be happy to replace it or refund your money.

You have our word on it.

principal display panel

H-E-B®

DANDRUFF 2-IN-1

SHAMPOO + CONDITIONER

WITH PYRITHIONE ZINC

CLEAN APPLE

REFRESHING AND CLEAN

Leaves Hair Healthy-Looking & HELPS RELIEVE DRY SCALP

12.5 FL OZ (370 mL)